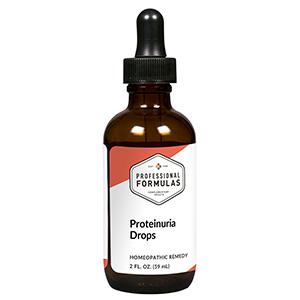 DRUG LABEL: Proteinuria Drops
NDC: 63083-2053 | Form: LIQUID
Manufacturer: Professional Complementary Health Formulas
Category: homeopathic | Type: HUMAN OTC DRUG LABEL
Date: 20190815

ACTIVE INGREDIENTS: BERBERIS VULGARIS ROOT BARK 6 [hp_X]/59 mL; EQUISETUM ARVENSE TOP 6 [hp_X]/59 mL; BEEF KIDNEY 6 [hp_X]/59 mL; RHODODENDRON TOMENTOSUM LEAFY TWIG 12 [hp_X]/59 mL; PHOSPHORUS 12 [hp_X]/59 mL; ALBUMIN HUMAN 12 [hp_X]/59 mL
INACTIVE INGREDIENTS: ALCOHOL; WATER

C53

ACTIVE INGREDIENTS

Berberis vulgaris 6X
Equisetum arvense 6X
Kidney 6X, 12X
Ledum palustre 12X
Phosphorus 12X
Albumin 12X, 30X

QUESTIONS

Professional Formulas

PO Box 2034 Lake Oswego, OR 97035

INDICATIONS

For the temporary relief of mild pain in the back or abdomen, bloating, foaming urine, or swelling of small joints.*

PURPOSE

*Claims based on traditional homeopathic practice, not accepted medical evidence. Not FDA evaluated.

WARNINGS

Consult a doctor if condition worsens, if symptoms persist, or are accompanied by fever, vomiting, or bloody urine. Keep out of the reach of children. In case of overdose, get medical help or contact a poison control center right away. If pregnant or breastfeeding, ask a healthcare professional before use.

Keep out of the reach of children.

PREGNANCY OR BREAST FEEDING

If pregnant or breastfeeding, ask a healthcare professional before use.

DIRECTIONS

Place drops under tongue 30 minutes before/after meals. Adults and children 12 years and over: Take 10 drops up to 3 times per day. Consult a physician for use in children under 12 years of age.

OTHER INFORMATION

Tamper resistant. If seal is broken, do not use. After opening, close container tightly and store at room temperature away from heat.

INACTIVE INGREDIENTS

20% ethanol, purified water.

LABEL

Est 1985

Professional Formulas

Complementary Health

Proteinuria Drops

Homeopathic Remedy

2 FL. OZ. (59 mL)